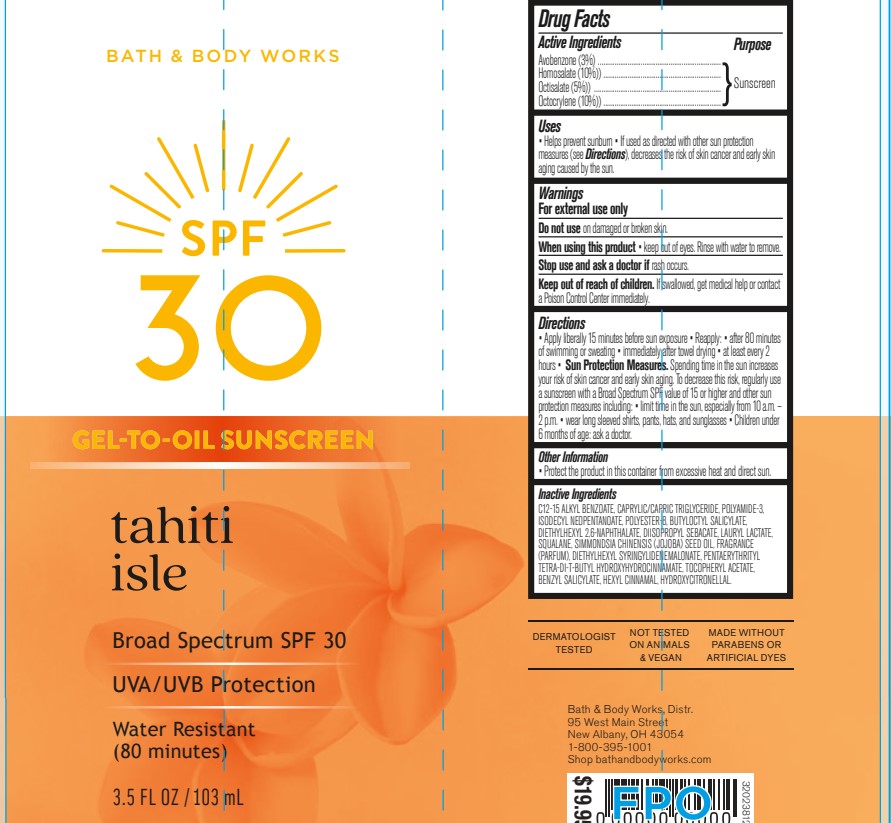 DRUG LABEL: Bath and Body Works SPF
NDC: 62670-6864 | Form: GEL
Manufacturer: Bath & Body Works, Inc.
Category: otc | Type: HUMAN OTC DRUG LABEL
Date: 20250630

ACTIVE INGREDIENTS: OCTOCRYLENE 10 mg/100 mg; AVOBENZONE 3 mg/100 mg; HOMOSALATE 10 mg/100 mg; OCTISALATE 5 mg/100 mg
INACTIVE INGREDIENTS: WATER

Bath & Body Works SPF 30 Gel To Oil Sunscreen Tahiti Isle

Active Ingredients

Avobenzone 3%, Homosalate 10%, Octisalate 5%, Octocrylene 10%

Purpose

Sunscreen

Uses

• helps prevent sunburn • if used as directed with other sun protection measures (see Directions), decreases the risk of skin cancer and early skin aging caused by the sun

Warnings

For external use only

Do not use

on damaged or broken skin

When using this product

keep out of eyes. Rinse with water to remove.

Stop use and ask a doctor

if rash occurs

Keep out of reach of children

If product is swallowed, get medical help or contact a Poison Control Center immediately.

Directions

• apply liberally 15 minutes before sun exposure • reapply: • after 80 minutes of swimming or sweating • immediately after towel drying • at least every 2 hours • Sun Protection Measures. Spending time in the sun increases your risk of skin cancer and early skin aging. To decrease this risk, regularly use a sunscreen with a broad spectrum SPF of 15 or higher and other sun protection measures including: • limit time in the sun, especially from 10 a.m. - 2 p.m. • wear long-sleeved shirts, pants, hats, and sunglasses • children under 6 months: Ask a doctor

Inactive ingredients

INACTIVE INGREDIENTS: C12-15 Alkyl Benzoate, Caprylic/Capric Triglyceride, Polyamide-3, Isodecyl Neopentanoate, Polyester-8, Butyloctyl Salicylate, Diethylhexyl 2,6-Naphthalate, Diisopropyl Sebacate, Lauryl Lactate, Squalane, Simmondsia Chinensis (Jojoba) Seed Oil, Fragrance (Parfum), Diethylhexyl Syringylidenemalonate, Pentaerythrityl Tetra-di-t-butyl Hydroxyhydrocinnamate, Tocopheryl Acetate, Benzyl Salicylate, Hexyl Cinnamal, Hydroxycitronellal.

Other information

• protect this product from excessive heat and direct sun

Bath & Body Works, Distr.

95 West Main Street New Albany, OH 43054

1-800-395-1001

shop bathandbodyworks.com